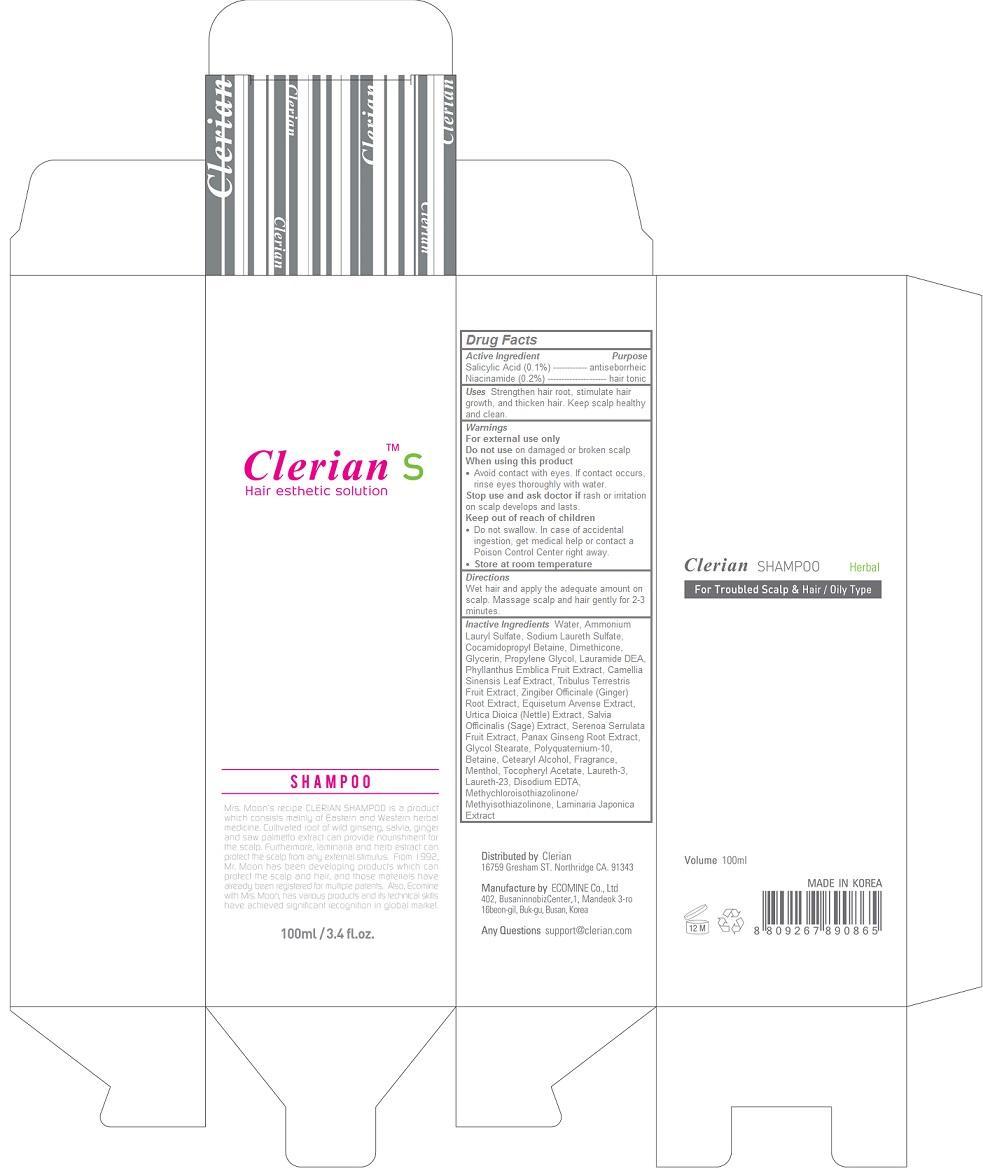 DRUG LABEL: Clerian
NDC: 69767-103 | Form: SHAMPOO
Manufacturer: CLERIAN, INC.
Category: otc | Type: HUMAN OTC DRUG LABEL
Date: 20150420

ACTIVE INGREDIENTS: NIACINAMIDE 0.2 1/100 mL; SALICYLIC ACID 0.1 1/100 mL
INACTIVE INGREDIENTS: WATER; Ammonium Lauryl Sulfate; Sodium Laureth Sulfate; Cocamidopropyl Betaine; Dimethicone; Glycerin; Propylene Glycol; LAURIC DIETHANOLAMIDE; PHYLLANTHUS EMBLICA FRUIT; GREEN TEA LEAF; TRIBULUS TERRESTRIS FRUIT; GINGER; EQUISETUM ARVENSE BRANCH; URTICA DIOICA LEAF; SALVIA OFFICINALIS ROOT; SAW PALMETTO; ASIAN GINSENG; Glycol Stearate; POLYQUATERNIUM-10 (1000 MPA.S AT 2%); Betaine; CETOSTEARYL ALCOHOL; Menthol; .ALPHA.-TOCOPHEROL ACETATE; LAURETH-3; Laureth-23; EDETATE DISODIUM; METHYLCHLOROISOTHIAZOLINONE; METHYLISOTHIAZOLINONE; LAMINARIA JAPONICA

Clerian Shampoo